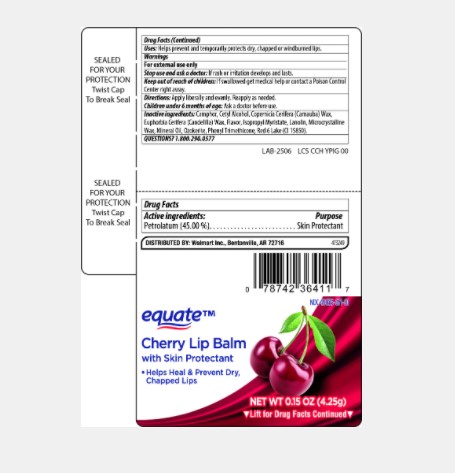 DRUG LABEL: Equate Cherry Lip Balm
NDC: 49035-671 | Form: STICK
Manufacturer: Walmart
Category: otc | Type: HUMAN OTC DRUG LABEL
Date: 20201212

ACTIVE INGREDIENTS: PETROLATUM 45.0 mg/1 g
INACTIVE INGREDIENTS: LIGHT MINERAL OIL 25.0 mg/1 g; MICROCRYSTALLINE WAX 3.00 mg/1 g; LANOLIN 1 mg/1 g; CERESIN 17.50 mg/1 g; CARNAUBA WAX 1 mg/1 g; ISOPROPYL MYRISTATE 2.33 mg/1 g

Drug Facts

Active ingredient

White Petrolatum

Purpose

Skin Protectant

Keep Out of Reach of Children

If swallowed get medical help or contact a Poison Control Center right away.

Uses

Helps prevent and temporarily protects dry, chapped, or wind burned lips.

Warnings

For external use only: Stop use and ask a doctor: if rash or irritation develops and lasts.

Directions

Apply liberally and as needed.

Children under 6 months of age: Ask a doctor before use.

Inactive Ingredients

Mineral Oil, Ozokerite, Flavor, Microcrystalline Wax, Isopropyl Myristate, Phenyl Trimethicone, Copernicia Cerifera (Carnauba) Wax, Lanolin, Euphorbia Cerifera (Candelilla) Wax, Cetyl Alcohol, Camphor, Red 6 Lake (CI 15850)